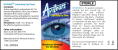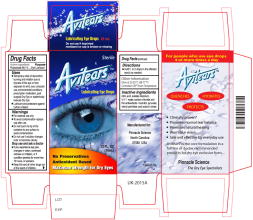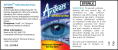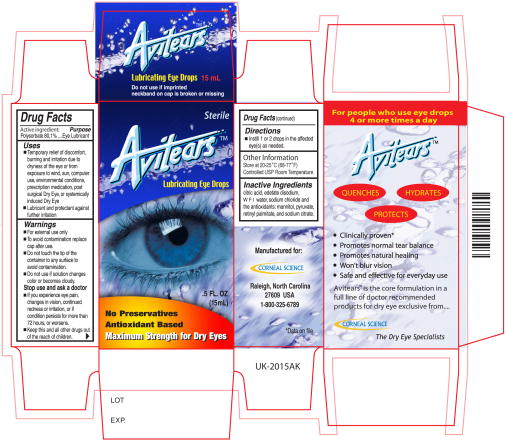 DRUG LABEL: Avitears
NDC: 49869-002 | Form: SOLUTION/ DROPS
Manufacturer: Pinnacle Science, LLc
Category: otc | Type: HUMAN OTC DRUG LABEL
Date: 20090831

ACTIVE INGREDIENTS: polysorbate 80 10 mg/1 mL
INACTIVE INGREDIENTS: sodium citrate; sodium chloride; citric acid monohydrate; mannitol; EDETATE DISODIUM

Avitears Lubricating Eye Drops

Active Ingredient

Polysorbate 80, 1%

Purpose

Lubricant

Uses

- Temporary relief of discomfort, burning and irritation due to dryness of the eye or from exposure to wind, sun, computer use, environmental conditions, prescription medication, post-surgical dry eye or systemically induced dry eye.
- Lubricant and protectant from further irritation

Warnings

- For external use only
- To avoid contamination replace cap after use
- Do not touch the tip of the container to any surface to avoid contamination
- Do not use if solution changes color or becomes cloudy

Stop use and ask a doctor

- If you experience eye pain, changes in vision, continued redness or irritation, or if condition persists for more than 72 hours or worsens
- Keep this and all other drugs out of the reach of children

Directions

- Instill one or two drops in the affected eye(s) as needed

Other Information

Store at 20 to 25° C (68 to 77° F)

Controlled USP Room Temperature

Inactive Ingredients

Citric acid, edetate disodium, WFI water, sodium chloride and the antioxidants: mannitol, pyruvate, retinyl palmitate and sodium citrate.

Principal Display Panel 10mL Bottle Label

AvitearsTM

Lubrication Eye Drops

0.33 FL.OZ

(10mL)

Maximum Strength for Dry Eyes

Principal Display Panel 10mL Carton Label

Sterile

AvitearsTM

Lubrication Eye Drops

.33 FL.OZ

(10mL)

No Preservatives

Antioxidant Based

Maximum Strength for Dry Eyes

Principal Display Panel 15mL Bottle Label

AvitearsTM

Lubrication Eye Drops

0.5 FL.OZ

(15mL)

Maximum Strength for Dry Eyes

Principal Display Panel 15mL Carton Label

Sterile

AvitearsTM

Lubrication Eye Drops

.5 FL.OZ

(15mL)

No Preservatives

Antioxidant Based

Maximum Strength for Dry Eyes